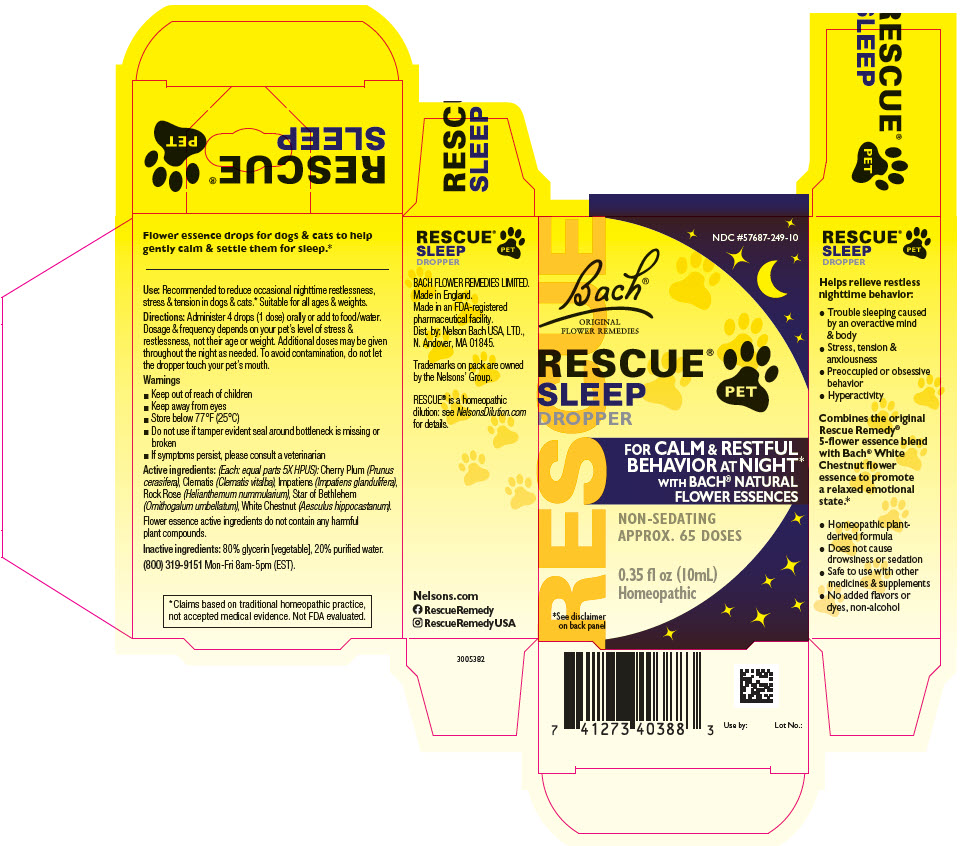 DRUG LABEL: Rescue Pet Sleep Dropper
NDC: 57687-249 | Form: LIQUID
Manufacturer: Nelson Bach USA Ltd
Category: homeopathic | Type: OTC ANIMAL DRUG LABEL
Date: 20240424

ACTIVE INGREDIENTS: PRUNUS CERASIFERA FLOWER 5 [hp_X]/10 mL; CLEMATIS VITALBA FLOWER 5 [hp_X]/10 mL; IMPATIENS GLANDULIFERA FLOWER 5 [hp_X]/10 mL; HELIANTHEMUM NUMMULARIUM FLOWER 5 [hp_X]/10 mL; ORNITHOGALUM UMBELLATUM FLOWERING TOP 5 [hp_X]/10 mL; AESCULUS HIPPOCASTANUM FLOWER 5 [hp_X]/10 mL
INACTIVE INGREDIENTS: Glycerin; WATER

Rescue® Pet Sleep Dropper

Flower essence drops for dogs & cats to help gently calm & settle them for sleep.*

VETERINARY INDICATIONS

Use: Recommended to reduce occasional nighttime restlessness, stress & tension in dogs & cats.* Suitable for all ages & weights.

DOSAGE AND ADMINISTRATION

Directions: Administer 4 drops (1 dose) orally or add to food/water. Dosage & frequency depends on your pet's level of stress & restlessness, not their age or weight. Additional doses may be given throughout the night as needed. To avoid contamination, do not let the dropper touch your pet's mouth.

Warnings

- Keep out of reach of children
- Keep away from eyes
- Store below 77°F (25°C)
- Do not use if tamper evident seal around bottleneck is missing or broken
- If symptoms persist, please consult a veterinarian

ACTIVE INGREDIENT

Active ingredients: (Each: equal parts 5X HPUS): Cherry Plum (Prunus cerasifera), Clematis (Clematis vitalba), Impatiens (Impatiens glandulifera), Rock Rose (Helianthemum nummularium), Star of Bethlehem (Ornithogalum umbellatum), White Chestnut (Aesculus hippocastanum).

Flower essence active ingredients do not contain any harmful plant compounds.

Inactive ingredients: 80% glycerin [vegetable], 20% purified water.

QUESTIONS

(800) 319-9151 Mon-Fri 8am-5pm (EST).

* Claims based on traditional homeopathic practice, not accepted medical evidence. Not FDA evaluated.

Helps relieve restless nighttime behavior:

- Trouble sleeping caused by an overactive mind & body
- Stress, tension & anxiousness
- Preoccupied or obsessive behavior
- Hyperactivity

Combines the original Rescue Remedy® 5-flower essence blend with Bach® White Chestnut flower essence to promote a relaxed emotional state.*

- Homeopathic plant-derived formula
- Does not cause drowsiness or sedation
- Safe to use with other medicines & supplements
- No added flavors or dyes, non-alcohol

BACH FLOWER REMEDIES LIMITED.
Made in England.
Made in an FDA-registered
pharmaceutical facility.

Dist. by: Nelson Bach USA, LTD.,
N. Andover, MA 01845.

Trademarks on pack are owned
by the Nelsons' Group.

RESCUE® is a homeopathic
dilution: see NelsonsDilution.com
for details.

Nelsons.com
RescueRemedy
RescueRemedyUSA

PRINCIPAL DISPLAY PANEL - 10 mL Bottle Box

RESCUE

NDC #57687-249-10

Bach®
ORIGINAL
FLOWER REMEDIES

RESCUE®
SLEEP
DROPPER

PET

FOR CALM & RESTFUL
BEHAVIOR AT NIGHT*
WITH BACH® NATURAL
FLOWER ESSENCES

NON-SEDATING
APPROX. 65 DOSES

0.35 fl oz (10mL)
Homeopathic

*See disclaimer
on back panel